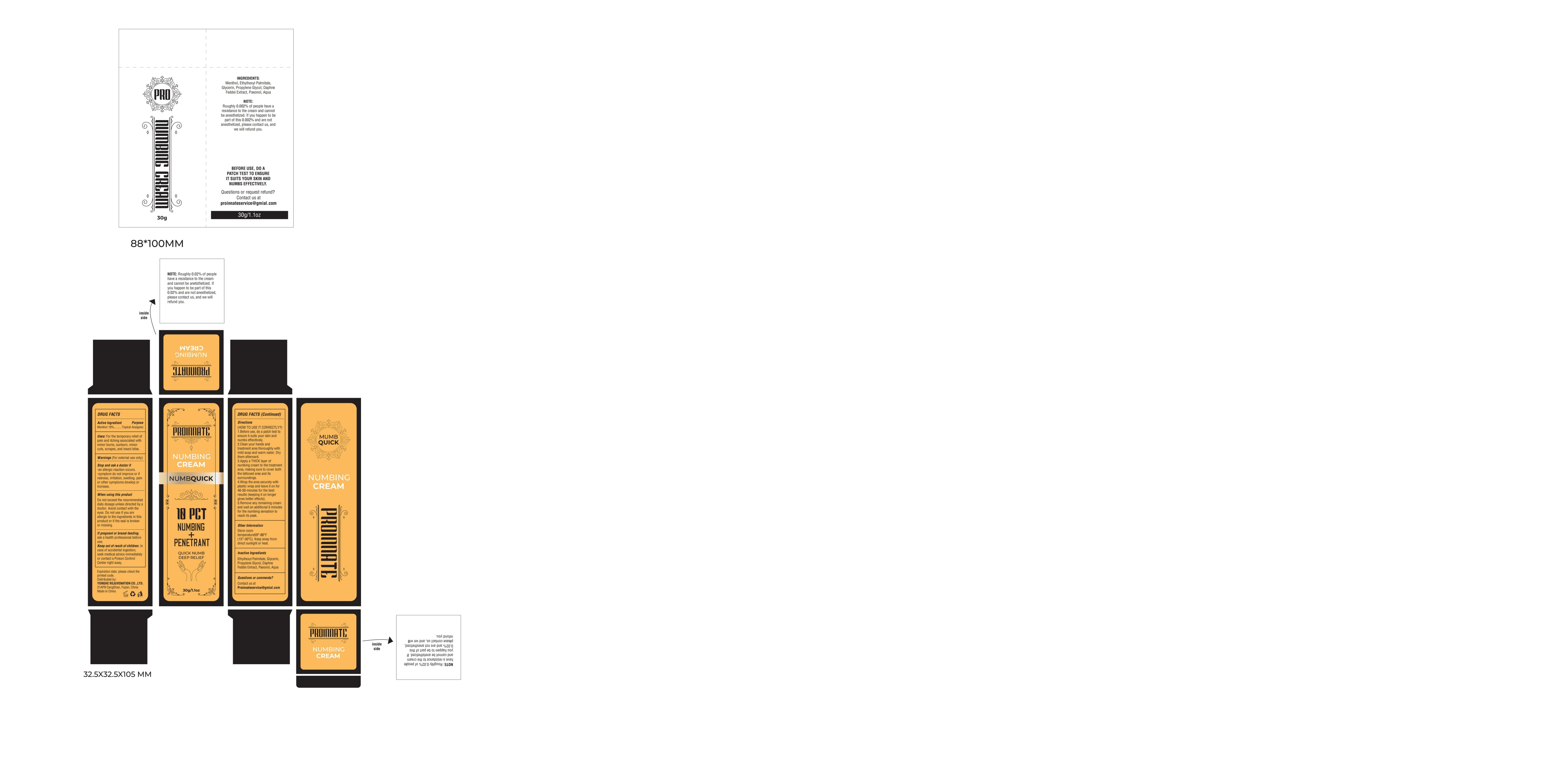 DRUG LABEL: PROINNATE Numbing Cream
NDC: 60771-0039 | Form: CREAM
Manufacturer: Guangzhou Haishi Biological Technology Co., Ltd.
Category: otc | Type: HUMAN OTC DRUG LABEL
Date: 20251013

ACTIVE INGREDIENTS: MENTHOL 10 g/100 g
INACTIVE INGREDIENTS: DAPHNETIN; PROPYLENE GLYCOL; GLYCERIN; AQUA; ETHYLHEXYL PALMITATE; PAEONOL

PROINNATE NUMBING CREAM

Active Ingredients

Menthol 10%

Purpose

For the temporary relief ofpain and itching associated withminor burns, sunburn, minorcuts, scrapes, and insect bites.

Uses

1.Before use, do a patch test toensure it suits your skin andnumbs effecitively.
2.Clean your hands andtreatment area thoroughly withmild soap and warm water. Drythem afterward.
3.Apply a THICK layer ofnumbing cream to the treatmentarea, making sure to cover boththe tattooed area and itssurroundings.4.Wrap the area securely withplastic wrap and leave it on for40-50 minutes for the bestresults (keeping it on longergives better effects).5.Remove any remaining creamand wait an additional 5 minutesfor the numbing sensation toreach its peak.

Warnings

For extemal use only

Stop Use

Stop and ask a doctor if-an allergic reaction occurs.-symptom do not improve or ifredness, irritation, swelling. painor other symptoms develop orincrease.

Do Not Use

Do not exceed the recommendeddaily dosage unless directed by adoctor. Avoid contact with theeyes. Do not use if you areallergic to the ingredients in thisproduct or if the seal is brokenor missing.

When Using

If pregnant or breast-feeding,ask a health professional beforeuse.

Keep Out Of Reach Of Children

Keep out ofreach of children. incase of accidental ingestion,seek medical advice immediatelyor contact a Poison ControlCenter right away.

Inactive ingredients

Aqua 74.5%
Ethylhexyl Palmitate 3%
Glycerin 5%
Propylene Glycol 5%
DaphneFeddei Extract 2%
Paeonol 0.5%

Dosage & administration

Apply a THiCK layer ofnumbing cream to the treatmentarea, making sure to cover boththe tattooed area and itssurroundings